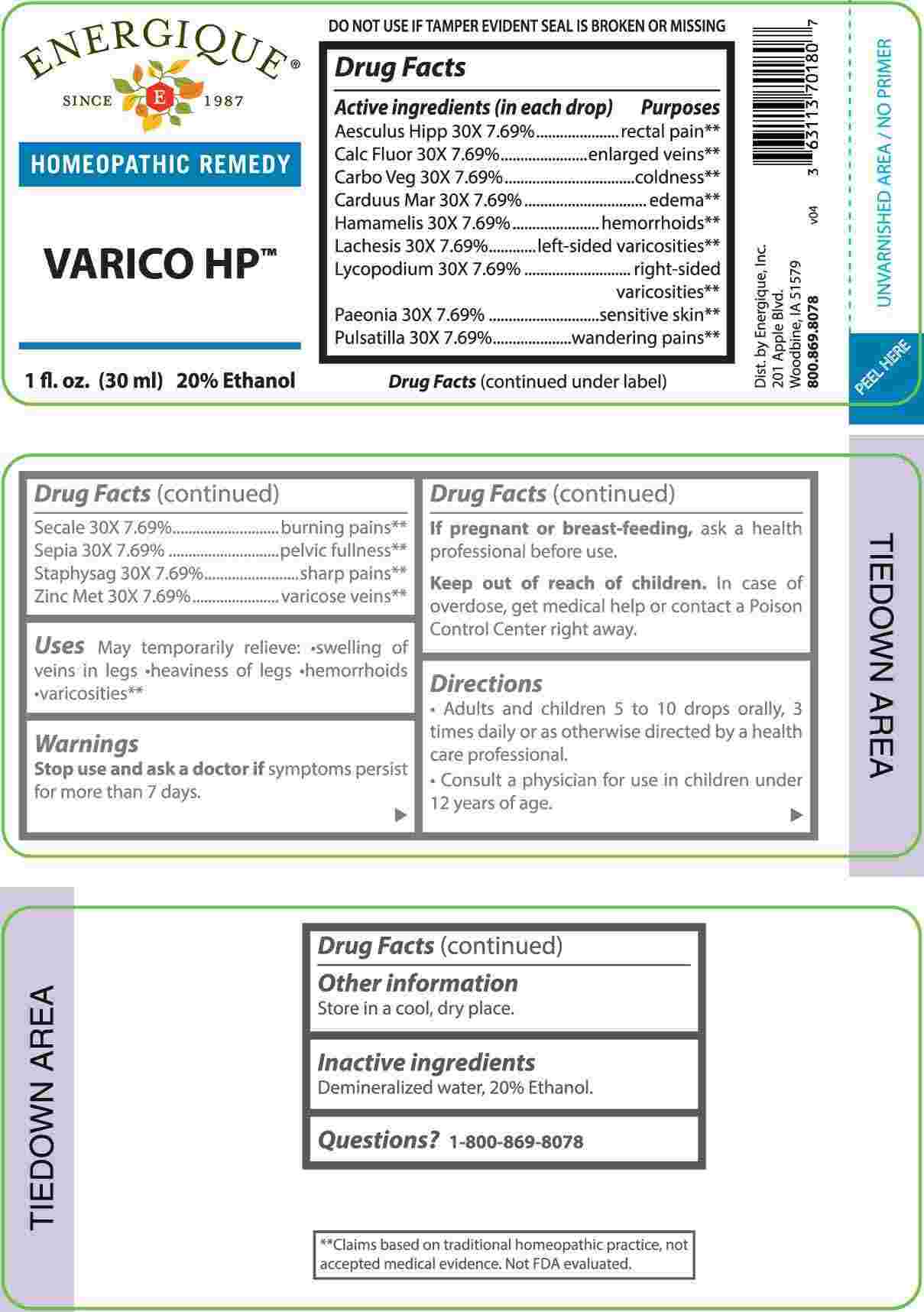 DRUG LABEL: Varico
NDC: 44911-0667 | Form: LIQUID
Manufacturer: Energique, Inc.
Category: homeopathic | Type: HUMAN OTC DRUG LABEL
Date: 20240508

ACTIVE INGREDIENTS: HORSE CHESTNUT 30 [hp_X]/1 mL; CALCIUM FLUORIDE 30 [hp_X]/1 mL; ACTIVATED CHARCOAL 30 [hp_X]/1 mL; MILK THISTLE 30 [hp_X]/1 mL; HAMAMELIS VIRGINIANA ROOT BARK/STEM BARK 30 [hp_X]/1 mL; LACHESIS MUTA VENOM 30 [hp_X]/1 mL; LYCOPODIUM CLAVATUM SPORE 30 [hp_X]/1 mL; PAEONIA OFFICINALIS ROOT 30 [hp_X]/1 mL; PULSATILLA PRATENSIS WHOLE 30 [hp_X]/1 mL; CLAVICEPS PURPUREA SCLEROTIUM 30 [hp_X]/1 mL; SEPIA OFFICINALIS JUICE 30 [hp_X]/1 mL; DELPHINIUM STAPHISAGRIA SEED 30 [hp_X]/1 mL; ZINC 30 [hp_X]/1 mL
INACTIVE INGREDIENTS: WATER; ALCOHOL

DRUG FACTS:

ACTIVE INGREDIENTS:

(in each drop) Aesculus Hippocastanum 30X 7.69%, Calcarea Fluorica 30X 7.69%, Carbo Vegetabilis 30X 7.69%, Carduus Marianus 30X 7.69%, Hamamelis Virginiana 30X 7.69%, Lachesis Mutus 30X 7.69%, Lycopodium Clavatum 30X 7.69%, Paeonia Officinalis 30X 7.69%, Pulsatilla 30X 7.69%, Secale Cornutum 30X 7.69%, Sepia 30X 7.69%, Staphysagria 30X 7.69%, Zincum Metallicum 30X 7.69%.

PURPOSES:

Aesculus Hippocastanum – rectal pain,** Calcarea Fluorica – enlarged veins,** Carbo Vegetabilis – coldness,** Carduus Marianus – edema,** Hamamelis Virginiana – hemorrhoids,** Lachesis Mutus – left-sided varicosities,** Lycopodium Clavatum – right-sided varicosities,** Paeonia Officinalis – sensitive skin,** Pulsatilla – wandering pains,** Secale Cornutum – burning pains,** Sepia – pelvic fullness,** Staphysagria – sharp pains,** Zincum Metallicum – varicose veins**

**Claims based on traditional homeopathic practice, not accepted medical evidence. Not FDA evaluated.

USES:

May temporarily relieve:

• swelling of veins in legs • heaviness of legs • hemorrhoids •varicosities**

**Claims based on traditional homeopathic practice, not accepted medical evidence. Not FDA evaluated.

WARNINGS:

Stop use and ask a doctor if symptoms persist for more than 7 days.

If pregnant or breast-feeding, ask a health professional before use.

Keep out of reach of children. In case of overdose, get medical help or contact a Poison Control Center right away.

DO NOT USE IF TAMPER EVIDENT SEAL IS BROKEN OR MISSING

Store in a cool, dry place.

KEEP OUT OF REACH OF CHILDREN:

In case of overdose, get medical help or contact a Poison Control Center right away.

DIRECTIONS:

• Adults and children 5 to 10 drops orally, 3 times daily or as otherwise directed by a health care professional.

• Consult a physician for use in children under 12 years of age.

INACTIVE INGREDIENTS:

Demineralized water, 20% Ethanol.

QUESTIONS:

Dist. by Energique, Inc.

201 Apple Blvd

Woodbine, IA 51579

800.869.8078

PACKAGE LABEL DISPLAY:

ENERGIQUE

SINCE 1987

HOMEOPATHIC REMEDY

VARICO HP

1 fl. oz. (30 ml)